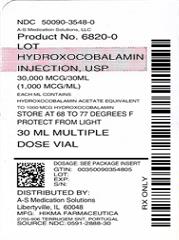 DRUG LABEL: Hydroxocobalamin
NDC: 50090-3548 | Form: INJECTION, SOLUTION
Manufacturer: A-S Medication Solutions
Category: prescription | Type: HUMAN PRESCRIPTION DRUG LABEL
Date: 20200118

ACTIVE INGREDIENTS: HYDROXOCOBALAMIN ACETATE 1000 ug/1 mL
INACTIVE INGREDIENTS: SODIUM ACETATE ANHYDROUS 0.2 mg/1 mL; ACETIC ACID 0.442 mg/1 mL; SODIUM CHLORIDE 8.2 mg/1 mL; METHYLPARABEN 1.5 mg/1 mL; PROPYLPARABEN 0.2 mg/1 mL; WATER

HYDROXOCOBALAMIN INJECTION USP
Rx Only

DESCRIPTION

Hydroxocobalamin injection is a sterile solution of hydroxocobalamin for intramuscular administration.

Each mL contains: Hydroxocobalamin Acetate equivalent to 1000 mcg Hydroxocobalamin, Sodium Acetate Anhydrous 0.2 mg, Glacial Acetic Acid 0.442 mg, Sodium Chloride 8.2 mg, with Methylparaben 1.5 mg and Propylparaben 0.2 mg as preservatives, in Water for Injection q.s. Additional Glacial Acetic Acid and/or Sodium Acetate may have been used to adjust pH. pH range is 3.5 to 5.0.

Hydroxocobalamin appears as dark red orthorhombic needles or as an amorphous or crystalline red powder. It is very hygroscopic in the anhydrous form, and moderately soluble in water. It has a molecular weight of 1346.37. The vitamin B12 coenzymes are very unstable in light. Hydroxocobalamin shares the cobalamin molecular structure with cyanocobalamin.

The chemical name is α-(5,6-dimethylbenzimidazoly) hydroxocobamide. The empirical formula is C62H89CoN13O15P and its structural formula is:

The cobalt content is 4.34%.

CLINICAL PHARMACOLOGY

Vitamin B12 is essential to growth, cell reproduction, hematopoiesis, nucleoprotein and myelin synthesis.

Fifty percent of the administered dose of hydroxocobalamin disappears from the injection site in 2.5 hours. Hydroxocobalamin is bound to plasma proteins and stored in the liver. It is excreted in the bile and undergoes some enterohepatic recycling. Within 72 hours after injection of 500 to 1000 mcg of hydroxocobalamin, 16 to 66 percent of the injected dose may appear in the urine. The major portion is excreted within the first 24 hours.

INDICATIONS AND USAGE

1. Pernicious anemia, both uncomplicated and accompanied by nervous system involvement.
2. Dietary deficiency of Vitamin B12, occurring in strict vegetarians and in their breast-fed infants. (Isolated vitamin B12 deficiency is very rare).
3. Malabsorption of vitamin B12, resulting from structural or functional damage to the stomach, where intrinsic factor is secreted or to the ileum, where intrinsic factor facilitates vitamin B12 absorption. These conditions include tropical sprue, and nontropical sprue (idiopathic steatorrhea, gluten-induced enteropathy). Folate deficiency in these patients is usually more severe than vitamin B12 deficiency.
4. Inadequate secretion of intrinsic factor, resulting from lesions that destroy the gastric mucosa (ingestion of corrosives, extensive neoplasia), and a number of conditions associated with a variable degree of gastric atrophy (such as multiple sclerosis, certain endocrine disorders, iron deficiency, and subtotal gastrectomy). Total gastrectomy always produces vitamin B12 deficiency.
  Structural lesions leading to vitamin B12 deficiency include regional ileitis, ileal resections, malignancies, etc.
5. Competition for Vitamin B12 by intestinal parasites or bacteria.
  The fish tapeworm (Diphyllobothrium latum) absorbs huge quantities of vitamin B12 and infested patients often have associated gastric atrophy. The blind-loop syndrome may produce deficiency of Vitamin B12 or folate.
6. Inadequate utilization of vitamin B12. This may occur if antimetabolites for the vitamin are employed in the treatment of neoplasia.
7. For the Schilling Test.

CONTRAINDICATION

Hypersensitivity to any component of this medication.

WARNINGS

Avoid the intravenous route.

Folic acid is not a substitute for vitamin B12 although it may improve vitamin B12 deficient megaloblastic anemia. Exclusive use of folic acid in treating vitamin B12 deficient megaloblastic anemia could result in progressive and irreversible neurologic damage.

Blunted or impeded therapeutic response to vitamin B12 may be due to such conditions as infection, uremia, drugs having bone marrow suppressant properties such as chloramphenicol, and concurrent iron or folic acid deficiency.

PRECAUTIONS

General

The validity of diagnostic vitamin B12 or folic acid blood assays could be compromised by medications, and this should be considered before relying on such tests for therapy.

Vitamin B12 is not a substitute for folic acid and since it might improve folic acid deficient megaloblastic anemia, indiscriminate use of vitamin B12 could mask the true diagnosis.

Hypokalemia and thrombocytosis could occur upon conversion of severe megaloblastic to normal erythropoiesis with B12 therapy. Therefore, serum potassium levels and the platelet count should be monitored carefully during therapy.

Vitamin B12 deficiency may suppress the signs of polycythemia vera. Treatment with vitamin B12 may unmask this condition.

Carcinogenesis, Mutagenesis, Impairment of Fertility

Studies of carcinogenicity, mutagenesis, or impairment of fertility have not been performed with hydroxocobalamin.

Pregnancy

Teratogenic Effects: Pregnancy Category C: Animal reproduction studies have not been conducted with hydroxocobalamin. It is also not known whether hydroxocobalamin can cause fetal harm when administered to a pregnant woman or can affect reproduction capacity. Hydroxocobalamin should be given to a pregnant woman only if clearly needed.

ADVERSE REACTIONS

Mild transient diarrhea, itching, transitory exanthema, feeling of swelling of entire body, and anaphylaxis.

A few patients may experience pain after injection of hydroxocobalamin.

To report SUSPECTED ADVERSE EVENTS, contact Actavis at 1-800-272-5525 or FDA at 1-800-FDA-1088 or http://www.fda.gov/ for voluntary reporting of adverse reactions.

OVERDOSAGE

The intravenous LD50 of hydroxocobalamin in mice is greater than 50 mL/kg.

DOSAGE AND ADMINISTRATION

Protect from light.

Parenteral drug products should be inspected visually for particulate matter and discoloration prior to administration, whenever solution and container permit.

Hydroxocobalamin injection should be given only intramuscularly.

In patients with Addisonian Pernicious Anemia, parenteral therapy with vitamin B12 is the recommended method of treatment and will be required for the remainder of the patient’s life. Oral therapy is not dependable. In other patients with vitamin B12 deficiency, the duration of therapy and route of administration will depend upon the cause and whether or not it is reversible.

Confirmatory diagnostic studies should be performed prior to initiating therapy, if possible, and the patient should be followed with appropriate studies to demonstrate hematologic improvement (Hgb, hematocrit, RBC, reticulocyte count). A diagnostic trial utilizing physiologic doses of vitamin B12 (1 mcg daily) and observing daily reticulocyte counts after establishing a baseline may also be performed. The observation of reticulocytosis which usually occurs between the third and tenth day of therapy confirms the diagnosis of vitamin B12 deficiency.

In seriously ill patients it may be advisable to administer both vitamin B12 and folic acid while awaiting the results of distinguishing laboratory studies. It is not necessary to withhold vitamin B12 therapy until the precise cause of B12 deficiency is established since absorption studies can be performed at any time.

Serum potassium should be closely observed the first 48 hours and potassium should be administered if necessary.

Treatment of Vitamin B12 Deficiency

Thirty mcg daily for 5 to 10 days followed by 100 to 200 mcg monthly injected intramuscularly. If the patient is critically ill, or has neurologic disease, an infectious disease or hyperthyroidism, considerably higher doses may be indicated. However, current data indicate that the optimum obtainable neurologic response may be expected with a dosage of vitamin B12 sufficient to produce good hematologic response. Children may be given a total of 1 to 5 mg over a period of 2 or more weeks in doses of 100 mcg, then 30 to 50 mcg every 4 weeks for maintenance.

Patients who have normal intestinal absorption may be treated with an oral therapeutic multivitamin preparation, containing 15 mcg vitamin B12 daily.

Schilling Test

The flushing dose is 1000 mcg.

HOW SUPPLIED

Product: 50090-3548

NDC: 50090-3548-0 30 mL in a VIAL, MULTI-DOSE / 1 in a CARTON

Storage

Manufactured by: Hikma Farmaceutica (Portugal) S.A. 2705-906 Terrugem SNT, PortugalStore at 20°-25°C (68°-77°F). [See USP controlled room temperature.] PROTECT FROM LIGHT.